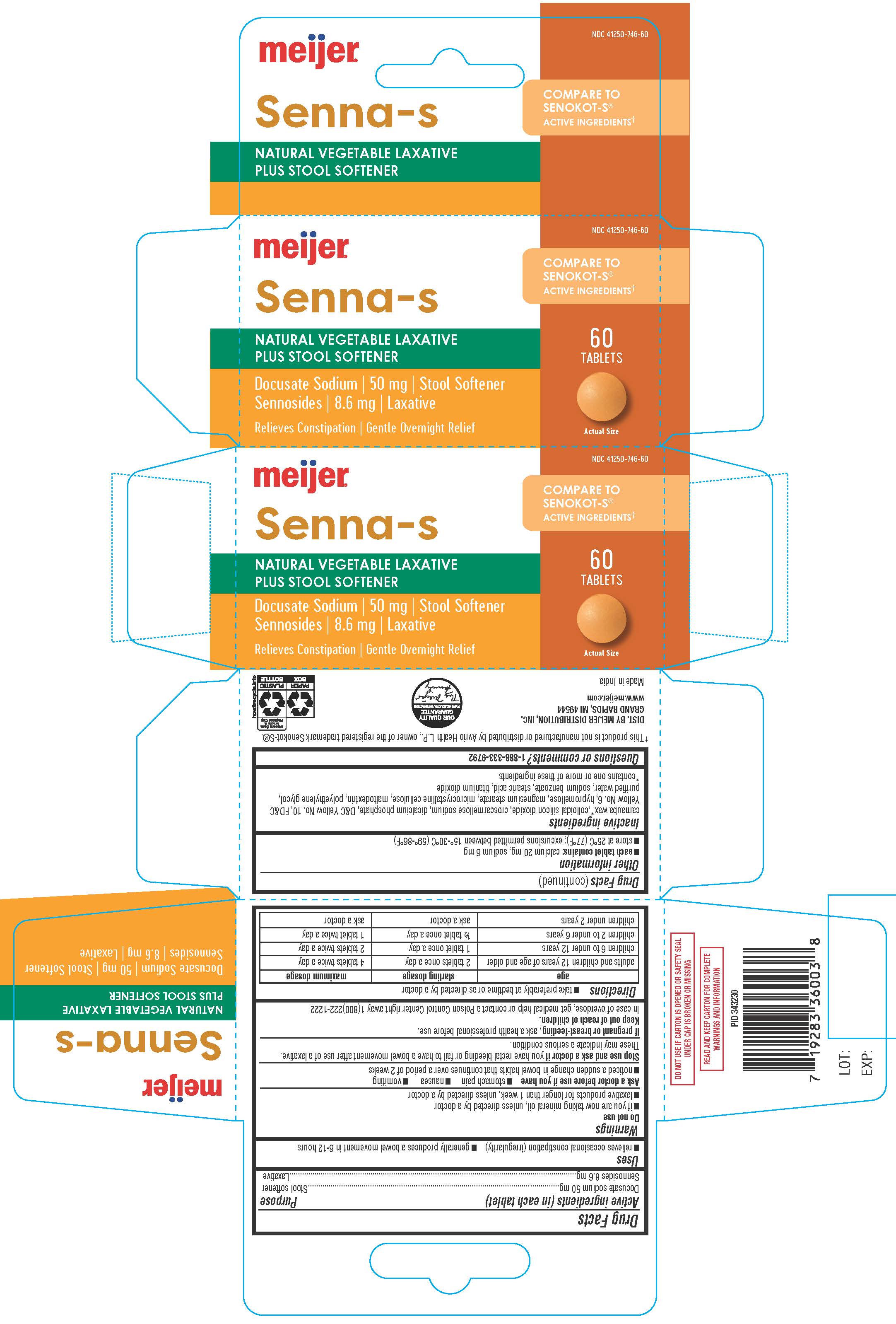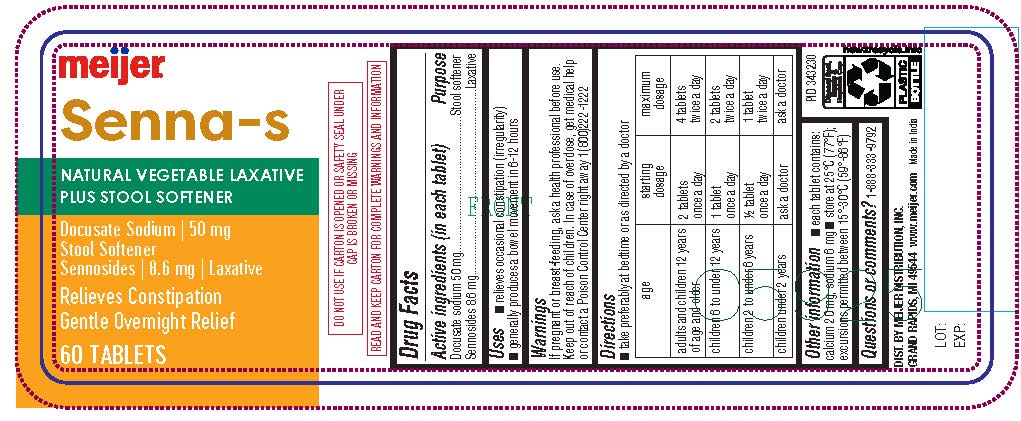 DRUG LABEL: SENNA-S
NDC: 41250-746 | Form: TABLET
Manufacturer: Meijer Distribution Inc.
Category: otc | Type: HUMAN OTC DRUG LABEL
Date: 20241220

ACTIVE INGREDIENTS: DOCUSATE SODIUM 50 mg/1 1; SENNOSIDES 8.6 mg/1 1
INACTIVE INGREDIENTS: SILICON DIOXIDE; CROSCARMELLOSE SODIUM; ANHYDROUS DIBASIC CALCIUM PHOSPHATE; D&C YELLOW NO. 10; FD&C YELLOW NO. 6; HYPROMELLOSES; MAGNESIUM STEARATE; MICROCRYSTALLINE CELLULOSE; MALTODEXTRIN; POLYETHYLENE GLYCOL 400; WATER; SODIUM BENZOATE; STEARIC ACID; TITANIUM DIOXIDE

Meijer SENNA-S Tablets

Drug Facts

Active ingredients (in each tablet)

Docusate sodium 50 mg

Sennosides 8.6 mg

Purpose

Stool softener

Laxative

Uses

- relieves occasional constipation (irregularity)
- generally produces bowel movement in 6-12 hours

Warnings

Do not use

- if you are now taking mineral oil, unless directed by a doctor
- laxative products for longer than 1 week, unless directed by a doctor

Ask a doctor before use if you have

- stomach pain
- nausea
- vomiting
- noticed a sudden change in bowel habits that continues over a period of 2 weeks

Stop use and ask a doctor if you have rectal bleeding or fail to have a bowel movement after use of a laxative. These may indicate a serious condition.

PREGNANCY OR BREAST FEEDING

If pregnant or breast-feeding, ask a health professional before use.

Keep out of reach of children.

in case of overdoese, get medical help or contact a Poison Control Center right away 1(800)222-1222

Directions

- take preferably at bedtime or as directed by a doctor

Age | Starting Dosage | Maximum Dosage
adults and children 12 years of age or older | 2 tablets once a day | 4 tablets twice a day
children 6 to under 12 years | 1 tablet once a day | 2 tablets twice a day
children 2 to under 6 years | ½ tablet once a day | 1 tablet twice a day
children under 2 years | ask a doctor | ask a doctor

Other information

- each tablet contains: calcium 19.92 mg, sodium 5.61 mg
- store at 25°C (77°F); excursions permitted between 15°-30°C (59°-86°F)

Inactive ingredients

Colloidal silicon dioxide, croscarmellose sodium, dicalcium phosphate, D&C Yellow No. 10, FD&C Yellow No. 6, hypromellose, magnesium stearate, microcrystalline cellulose, maltodextrin, polyethylene glycol-400, purified water, sodium benzoate, stearic acid, titanium dioxide

Questions or comments?

1-888-333-9792

PRINCIPAL DISPLAY PANEL

Compare to the active ingredients

in Senokot-S®*

Senna-S

DOCUSATE SODIUM 50 MG and SENNOSIDES 8.6 mg

NATURAL LAXATIVE

PLUS STOOL SOFTENER

60 TABLETS